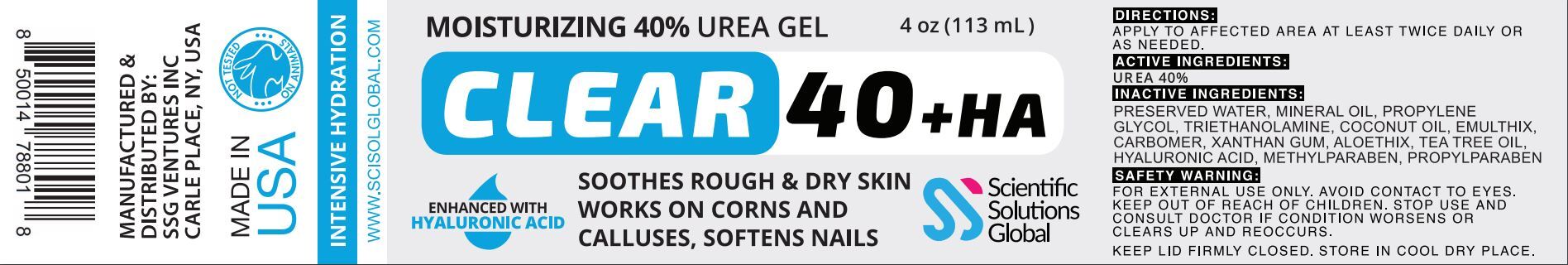 DRUG LABEL: Clear 40 Plus HA
NDC: 81376-233 | Form: GEL
Manufacturer: SSG Ventures Inc
Category: otc | Type: HUMAN OTC DRUG LABEL
Date: 20210427

ACTIVE INGREDIENTS: UREA 40 g/113 g
INACTIVE INGREDIENTS: CARBOXYPOLYMETHYLENE; XANTHAN GUM; MINERAL OIL; COCONUT OIL; WATER; TRIDECETH-10; TEA TREE OIL; PROPYLENE GLYCOL; ALOE VERA LEAF; HYALURONATE SODIUM

Clear 40 Plus HA

PACKAGE LABEL

ACTIVE INGREDIENTS:

UREA

PURPOSE

SOOTHES ROUGH & DRY SKIN

HEALS CORNS & CALLOUSES

SOFTENS NAILS

INDICATIONS AND USAGE

SOOTHES ROUGH & DRY SKIN

SAFE HANDLING WARNING

FOR EXTERNAL USE ONLY. AVOID CONTACT TO EYES.

KEEP OUT OF REACH OF CHILDREN. STOP USE AND CONSULT DOCTOR IF CONDITION WORSENS OR CLEARS UP AND REOCCURS.

KEEP LID FIRMLY CLOSED. STORE IN COOL DRY PLACE.

KEEP OUT OF REACH OF CHILDREN.

INSTRUCTIONS FOR USE

APPLY TO AFFECTED AREA AT LEAST TWICE DAILY OR AS NEEDED.

INACTIVE INGREDIENT

ALOE VERA, CARBOMER, COCONUT OIL, EMULSIFIERS, GREEN TEA, MINERAL OIL, PRESERVED WATER, POPYLENE GLYCOL, SODIUM HYALURONATE, TEA TREE OIL, TRIETHANOLOAMINE, XANTHAM GUM

STORAGE AND HANDLING

KEEP LID FIRMLY CLOSED. STORE IN COOL DRY PLACE.

OTHER SAFETY INFORMATION

ENHANCED WITH TEA TREE OIL & ALOE VERA

DOSAGE AND ADMINISTRATION

APPLY TO AFFECTED AREA AT LEAST TWICE DAILY OR AS NEEDED.USE CONTINUOUSLY FOR 2-3 WEEKS FOR OPTIMAL RESULTS.

WARNINGS

FOR EXTERNAL USE ONLY. AVOID CONTACT TO EYES. STOP USE AND CONSULT DOCTOR IF CONDITION WORSENS OR CLEARS UP AND REOCCURS.